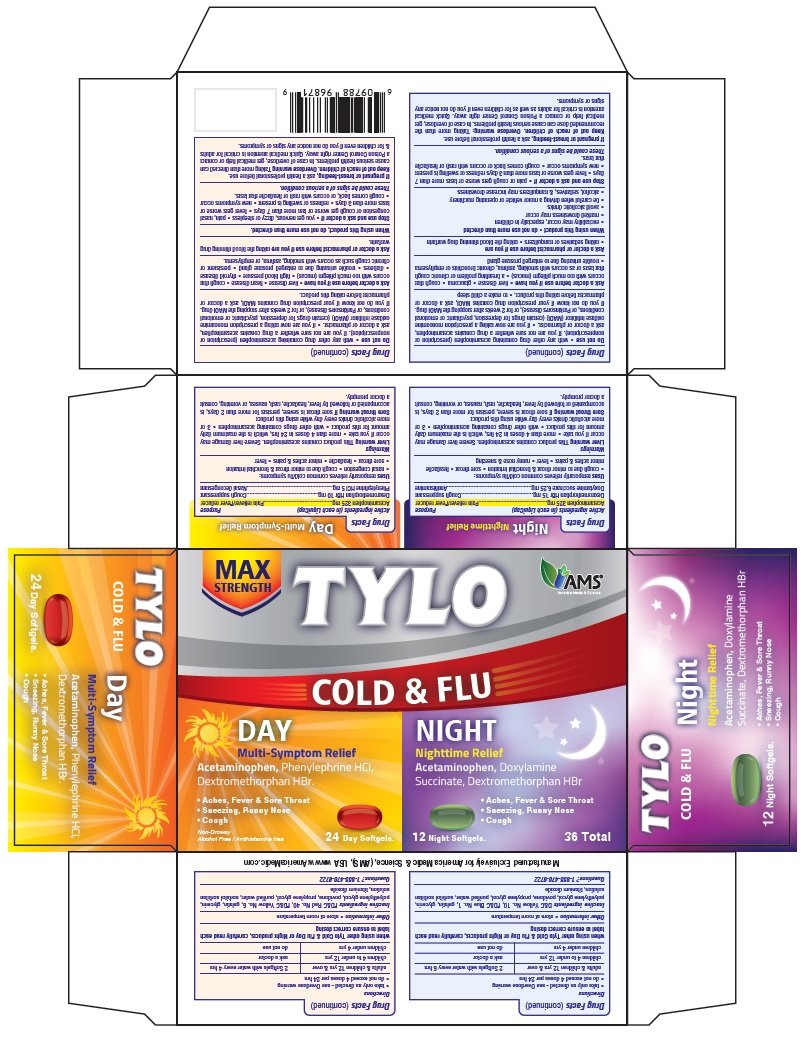 DRUG LABEL: Tylo Cold and Flu
NDC: 49638-114 | Form: CAPSULE, LIQUID FILLED
Manufacturer: America Medic & Science, LLC
Category: otc | Type: HUMAN OTC DRUG LABEL
Date: 20190122

ACTIVE INGREDIENTS: ACETAMINOPHEN 325 mg/1 1; DEXTROMETHORPHAN HYDROBROMIDE 15 mg/1 1; DOXYLAMINE SUCCINATE 6.25 mg/1 1
INACTIVE INGREDIENTS: D&C YELLOW NO. 10; FD&C BLUE NO. 1; GELATIN; GLYCERIN; POLYETHYLENE GLYCOL, UNSPECIFIED; POVIDONE; PROPYLENE GLYCOL; WATER; SORBITOL; TITANIUM DIOXIDE

TYLO COLD & FLU (Night)

Active ingredients (in each LiquiCap)

Acetaminophen 325 mg
Dextromethorphan HBr 15 mg
Doxylamine succinate 6.25 mg

Purpose

Pain reliever/fever reducer
Cough suppressant
Antihistamine

Uses

- temporarily relieves common cold/flu symptoms:
  - cough due to minor throat and bronchial irritation
  - sore throat
  - headache
  - minor aches & pains
  - fever
  - runny nose & sneezing

Warnings

Liver warning: This product contains acetaminophen. Severe liver damage may occur if you take

- more than 4 doses in 24 hrs, which is the maximum daily amount for this product
- with other drugs containing acetaminophen
- 3 or more alcoholic drinks every day while using this product

Sore throat warning If sore throat is severe, persists for more than 2 days, is accompanied or followed by fever, headache, rash, nausea, or vomiting, consult a doctor promptly.

Do not use

- with any other drug containing acetaminophen (prescription or nonprescription). If you are not sure whether a drug contains acetaminophen, ask a doctor or pharmacist.
- if you are now taking a prescription monoamine oxidase inhibitor (MAOI) (certain drugs for depression, psychiatric or emotional conditions, or Parkinson's disease), or for 2 weeks after stopping the MAOI drug. If you do not know if your prescription drug contains MAOI, ask a doctor or pharmacist before taking this product.

Ask a doctor before use if you have

- liver disease
- glaucoma
- cough that occurs with too much phlegm (mucus)
- a breathing problem or chronic cough that lasts or as occurs with smoking, asthma, chronic bronchitis or emphysema
- trouble urinating due to enlarged prostate gland

Ask a doctor or pharmacist before use if you are

- taking sedatives or tranquilizers
- taking the blood thinning drug warfarin

When using this product

do not use more than directed.

- excitability may occur, especially in children
- marked drowsiness may occur
- avoid alcoholic drinks
- be careful when driving a motor vehicle or operating machinery
- alcohol, sedatives, & tranquilizers may increase drowsiness

Stop use and ask a doctor if

- pain or cough gets worse or lasts more than 7 days
- fever gets worse or lasts more than 3 days redness or swelling is present
- new symptoms occur
- cough comes back or occurs with rash or headache that lasts.

These could be signs of a serious condition.

If pregnant or breast-feeding,

ask a health professional before use.

Other Information

Keep out of reach of children.

Overdose warning Taking more than directed can cause serious health problems. In case of overdose, get medical help or contact a Poison Control Center right away. Quick medical attention is critical for adults & for children even if you do not notice any signs or symptoms.

Directions

- take only as directed - see Overdose warning
- do not exceed 4 doses per 24 hrs
- adults & children 12 yrs & over: 2 Softgels with water every 6 hrs
- children 4 to under 12 yrs: ask a doctor
- children under 4 yrs: do not use

DOSAGE AND ADMINISTRATION

when using other Tylo Cold & Flu Day or Night products, carefully read each label to ensure correct dosing

Other information:

store at room temperature

Inactive ingredients

D&C Yellow No. 10, FD&C Blue No. 1, gelatin, glycerin, polyethylene glycol, povidone, propylene glycol, purified water, sorbitol sorbitan solution, titanium dioxide

Questions?

1-855-470-6722

PACKAGE LABEL

TYLO COLD & FLU (Night)

Acetaminophen 325 mg
Dextromethorphan HBr 15 mg
Doxylamine succinate 6.25 mg